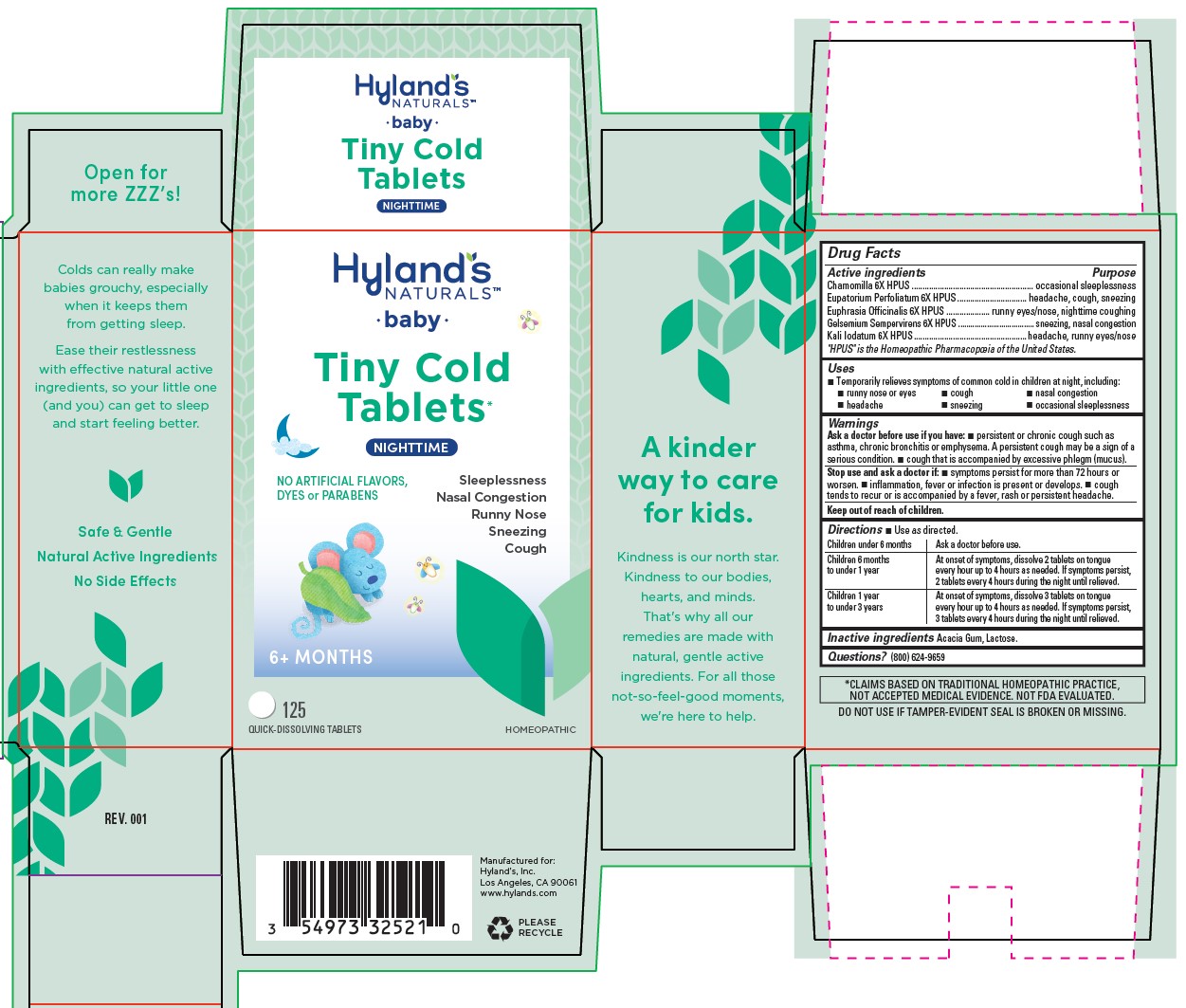 DRUG LABEL: Baby Nighttime Tiny Cold
NDC: 54973-3252 | Form: TABLET
Manufacturer: Hyland's
Category: homeopathic | Type: HUMAN OTC DRUG LABEL
Date: 20211227

ACTIVE INGREDIENTS: MATRICARIA RECUTITA 6 [hp_X]/1 1; EUPATORIUM PERFOLIATUM FLOWERING TOP 6 [hp_X]/1 1; EUPHRASIA STRICTA 6 [hp_X]/1 1; GELSEMIUM SEMPERVIRENS ROOT 6 [hp_X]/1 1; POTASSIUM IODIDE 6 [hp_X]/1 1
INACTIVE INGREDIENTS: ACACIA; LACTOSE, UNSPECIFIED FORM

Hyland's Naturals Baby Tiny Cold Tablets Nighttime

PURPOSE

Relieves nasal congestion, runny nose, sneezing, cough and occasional sleeplessness

Drug Facts

Active ingredients | Purpose
Chamomilla 6X HPUS | occasional sleeplessness
Eupatorium Perfoliatum 6X HPUS | headache, cough, sneezing
Euphrasia Officinalis 6X HPUS | runny eyes/nose, nighttime coughing
Gelsemium Sempervirens 6X HPUS | sneezing, nasal congestion,occasional sleeplessness
Kali Iodatum 6X HPUS | headache, runny eyes/nose

"HPUS" indicates that the active ingredients are in the official Homeopathic

Pharmacopoeia of the United States.

Uses

■ Temporarily relieves symptoms of common cold in children at night, including:

■ runny nose or eyes ■ cough ■ nasal congestion

■ headache ■ sneezing ■ occasional sleeplessness

Warnings

Ask a doctor before use if you have:

■ persistent or chronic cough such as asthma, chronic bronchitis or emphysema. A persistent cough may be a sign of a serious condition. ■ cough that is accompanied by excessive phlegm (mucus).

Stop use and ask a doctor if:

■ symptoms persist for more than 72 hours or worsen. ■ inflammation, fever or infection is present or develops. ■ cough tends to recur or is accompanied by a fever, rash or persistent headache.

Directions

■ Use as directed.

Children under 6 months | Ask a doctor before use.
Children 6 months to under 1 year | At onset of symptoms, dissolve 2 tablets on tongue every hour up to 4 hours as needed. If symptoms persist, 2 tablets every 4 hours during the night until relieved.
Children 1 year to under 3 years | At onset of symptoms, dissolve 3 tablets on tongue every hour up to 4 hours as needed. If symptoms persist, 3 tablets every 4 hours during the night until relieved.

Inactive ingredients

Acacia Gum, Lactose.

Questions?

(800) 624-9659

Indications and Usage (Uses) Dosage and Administration

■ Temporarily relieves symptoms of common cold in children at night, including:

■ runny nose or eyes ■ cough ■ nasal congestion

■ headache ■ sneezing ■ occasional sleeplessness

Directions

■ Use as directed.

Children under 6 months
Ask a doctor before use.
Children 6 months
to under 1 year
At onset of symptoms, dissolve 2 tablets on tongue every hour up to 4 hours as needed. If symptoms persist,
2 tablets every 4 hours during the night until relieved.
Children 1 year
to under 3 years
At onset of symptoms, dissolve 3 tablets on tongue every hour up to 4 hours as needed. If symptoms persist,
3 tablets every 4 hours during the night until relieved.

PRINCIPAL DISPLAY PANEL - 125 Tablet Bottle Carton

Hyland's

NATURALS™

•baby•

Tiny Cold

Tablets*

Nighttime

NO ARTIFICIAL FLAVORS,

DYES or PARABENS

Sleeplessness

Nasal Congestions

Runny Nose

Sneezing

Cough

6+ MONTHS

125

QUICK-DISSOLVING TABLETS

HOMEOPATHIC